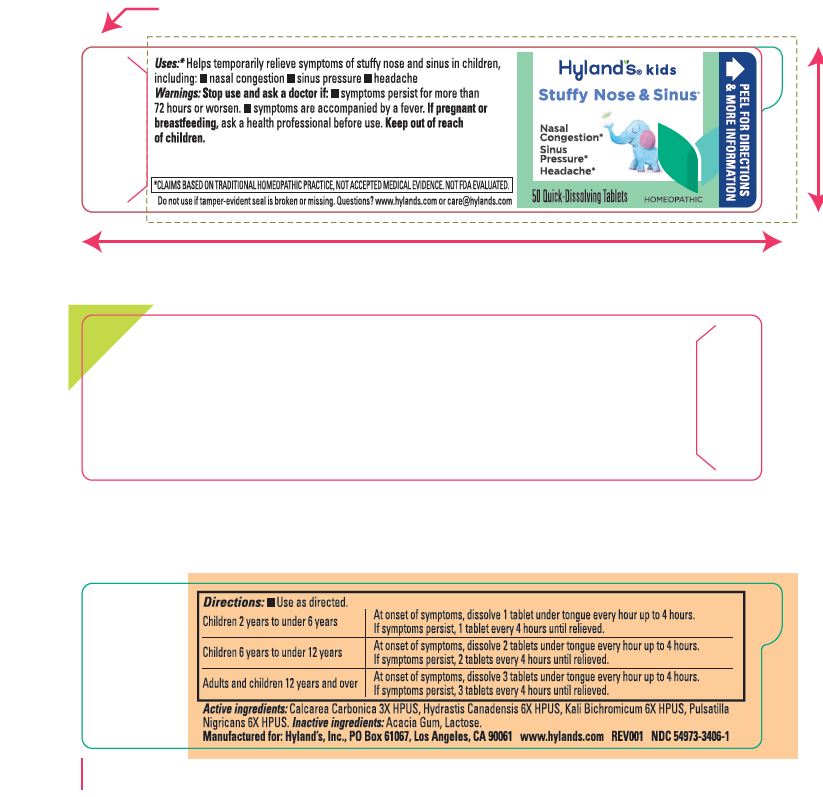 DRUG LABEL: 4 Kids Stuffy Nose and Sinus
NDC: 54973-3406 | Form: TABLET
Manufacturer: Hyland’s Inc.
Category: homeopathic | Type: HUMAN OTC DRUG LABEL
Date: 20250626

ACTIVE INGREDIENTS: OYSTER SHELL CALCIUM CARBONATE, CRUDE 3 [hp_X]/1 1; GOLDENSEAL 6 [hp_X]/1 1; POTASSIUM DICHROMATE 6 [hp_X]/1 1; PULSATILLA PRATENSIS WHOLE 6 [hp_X]/1 1
INACTIVE INGREDIENTS: ACACIA; LACTOSE MONOHYDRATE

Kids Stuffy Nose & Sinus

PURPOSE

Temporarily relieves symptoms of stuffy nose and sinus in children, including: nasal congestion, sinus pressure, headache

Drug Facts

Active ingredients

Active ingredients | Purpose
Calcarea Carbonica 3X HPUS | sinus pressure, congestion, headache
Hydrastis Canadensis 6X HPUS | sinus headache
Kali Bichromicum 6X HPUS | nasal congestion, sinus pressure
Pulsatilla Nigricans 6X HPUS | sinus pressure, headache

"HPUS" is the Homeopathic Pharmacopoeia of the United States.

Uses

■ Helps temporarily relieve symptoms of stuffy nose and sinus in children, including:

■ nasal congestion

■ sinus pressure

■ headache

Warnings

Stop use and ask a doctor if

■ symptoms persist for more than 72 hours or worsen. ■ symptoms are accompanied by a fever.

If pregnant or breastfeeding

ask a health professional before use.

Directions

■ Use as directed.

Children 2 years to under 6 years | At onset of symptoms, dissolve 1 tablet under tongue every hour up to 4 hours. If symptoms persist, 1 tablet every 4 hours until relieved.
Children 6 years to under 12 years | At onset of symptoms, dissolve 2 tablets under tongue every hour up to 4 hours. If symptoms persist, 2 tablets every 4 hours until relieved.
Adults and children 12 years and over | At onset of symptoms, dissolve 3 tablets under tongue every hour up to 4 hours. If symptoms persist, 3 tablets every 4 hours until relieved.

Inactive ingredients

Acacia Gum, Lactose.

Questions?

www.hylands.com or care@hylands.com

Indications and Usage

Uses

Helps temporarily relieve symptoms of stuffy nose and sinus in children, including:
nasal congestion sinus pressure headache

Principal Display Panel

Hyland's

•kids•

STUFFY NOSE

& SINUS*

NO ARTIFICIAL FLAVORS,
DYES or PARABENS

Nasal Congestion
Sinus Pressure
Headache

2- 12 YEARS

50

QUICK-DISSOLVING TABLETS

HOMEOPATHIC